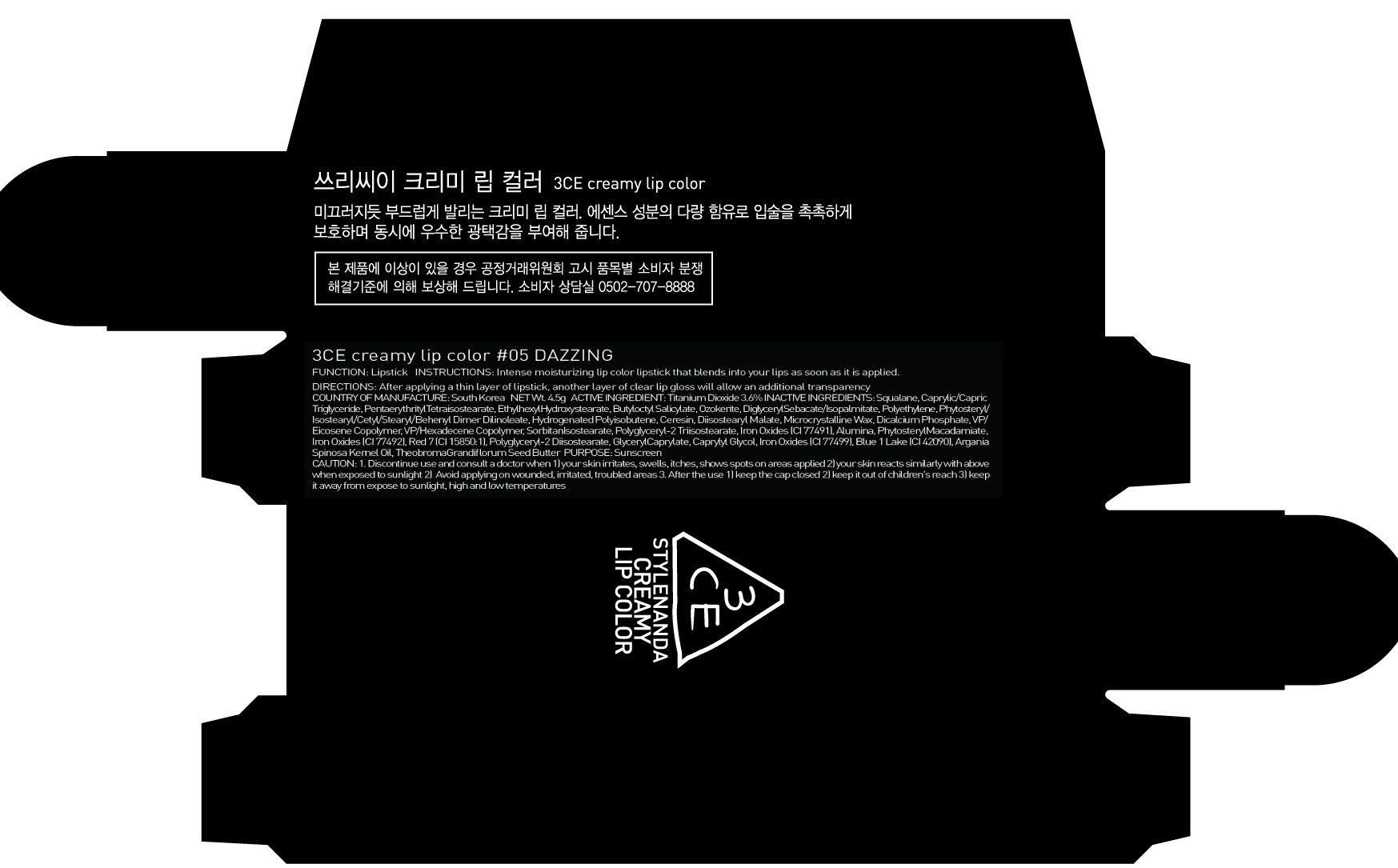 DRUG LABEL: 3CE CRE AMY LIP COLOR 05 DAZZLING
NDC: 60764-115 | Form: LIPSTICK
Manufacturer: Nanda Co., Ltd
Category: otc | Type: HUMAN OTC DRUG LABEL
Date: 20161014

ACTIVE INGREDIENTS: Titanium Dioxide 0.16 g/4.5 g
INACTIVE INGREDIENTS: Squalane; Pentaerythrityl Tetraisostearate

ACTIVE INGREDIENT

Active Ingredient: Titanium Dioxide 3.6%

INACTIVE INGREDIENT

Inactive Ingredients: Squalane, Caprylic/Capric Triglyceride, Pentaerythrityl Tetraisostearate, Ethylhexyl Hydroxystearate, Butyloctyl Salicylate, Ozokerite, DiglycerylSebacate/Isopalmitate, Polyethylene, Phytosteryl/Isostearyl/Cetyl/Stearyl/Behenyl Dimer Dilinoleate, Hydrogenated Polyisobutene, Ceresin, Diisostearyl Malate, Microcrystalline Wax, Dicalcium Phosphate, VP/Eicosene Copolymer, VP/Hexadecene Copolymer, SorbitanIsostearate, Polyglyceryl-2 Triisostearate, Iron Oxides (CI 77491), Alumina, PhytosterylMacadamiate, Iron Oxides (CI 77492), Red 7 (CI 15850:1), Polyglyceryl-2 Diisostearate, GlycerylCaprylate, Caprylyl Glycol, Iron Oxides (CI 77499), Blue 1 Lake (CI 42090), ArganiaSpinosa Kernel Oil, TheobromaGrandiflorum Seed Butter

PURPOSE

Purpose: Sunscreen

CAUTION

CAUTION: 1. Discontinue use and consult a doctor when - your skin irritates, swells, itches, shows spots on areas applied - your skin reacts similarly with above when exposed to sunlight 2. Avoid applying on wounded, irritated, troubled areas 3. After the use - keep the cap closed - keep it out of children's reach - keep it away from expose to sunlight, high and low temperatures

DESCRIPTION

INSTRUCTIONS: Intense moisturizing lip color lipstick that blends into your lips as soon as it is applied.

Directions: After applying a thin layer of lipstick, another layer of clear lip gloss will allow an additional transparency